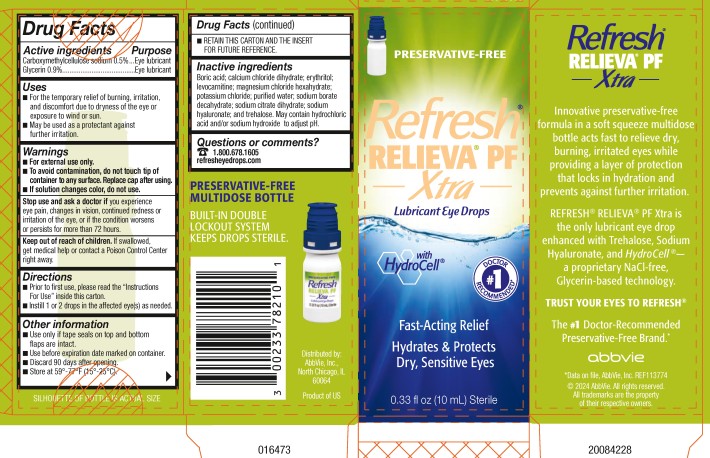 DRUG LABEL: Refresh Relieva PF Xtra
NDC: 0023-3782 | Form: SOLUTION/ DROPS
Manufacturer: Allergan, Inc.
Category: otc | Type: HUMAN OTC DRUG LABEL
Date: 20250915

ACTIVE INGREDIENTS: CARBOXYMETHYLCELLULOSE SODIUM 5 mg/1 mL; GLYCERIN 9 mg/1 mL
INACTIVE INGREDIENTS: BORIC ACID; CALCIUM CHLORIDE; ERYTHRITOL; LEVOCARNITINE; MAGNESIUM CHLORIDE; POTASSIUM CHLORIDE; WATER; SODIUM BORATE; TRISODIUM CITRATE DIHYDRATE; HYALURONATE SODIUM; TREHALOSE; HYDROCHLORIC ACID; SODIUM HYDROXIDE

REFRESH RELIEVA® PF XTRA
Drug Facts

Active ingredients

Carboxymethylcellulose sodium 0.5%
Glycerin 0.9%

Purpose

Eye lubricant
Eye lubricant

Uses

- For the temporary relief of burning, irritation, and discomfort due to dryness of the eye or exposure to wind or sun.
- May be used as a protectant against further irritation.

Warnings

- For external use only.
- To avoid contamination, do not touch tip of container to any surface. Replace cap after using.
- If solution changes color or becomes cloudy, do not use.

Stop use and ask a doctor if

you experience eye pain, changes in vision, continued redness or irritation of the eye, or if the condition worsens or persists for more than 72 hours.

Keep out of reach of children.

If swallowed, get medical help or contact a Poison Control Center right away.

Directions

- Prior to first use, please read the “Instructions For Use” inside this carton.
- Instill 1 or 2 drops in the affected eye(s) as needed.

Other information

- Use only if tape seals on top and bottom flaps are intact.
- Use before expiration date marked on container.
- Discard 90 days after opening.
- Store at 59°-77°F (15°-25°C).
- RETAIN THIS CARTON AND THE INSERT FOR FUTURE REFERENCE.

Inactive ingredients

Boric acid; calcium chloride dihydrate; erythritol; levocarnitine; magnesium chloride hexahydrate; potassium chloride; purified water; sodium borate decahydrate; sodium citrate dihydrate; sodium hyaluronate, and trehalose. May contain hydrochloric acid and/or sodium hydroxide (to adjust pH).

Questions or comments?

1.800.678.1605

refresheyedrops.com

v2.0DFL3782

PRINCIPAL DISPLAY PANEL

NDC 0023-3782-10

PRESERVATIVE-FREE
Refresh®
RELIEVA® PF
Xtra
Lubricant Eye Drops
With
HydroCell®
Fast-Acting Relief
Hydrates & Protects
Dry, Sensitive Eyes
0.33 fl oz (10 mL) Sterile